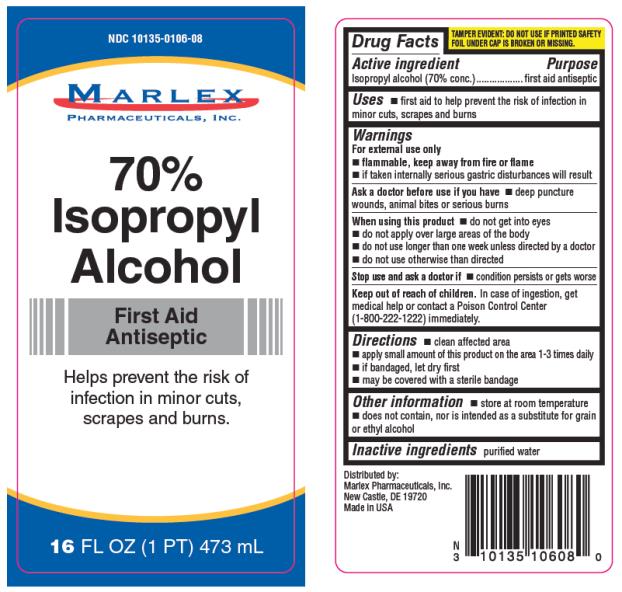 DRUG LABEL: Isopropyl Alcohol 70 Percent
NDC: 10135-106 | Form: LIQUID
Manufacturer: Marlex Pharmaceuticals Inc
Category: otc | Type: HUMAN OTC DRUG LABEL
Date: 20150801

ACTIVE INGREDIENTS: ISOPROPYL ALCOHOL 70 mL/100 mL
INACTIVE INGREDIENTS: WATER

Isopropyl Alcohol 70 Percent

Drug Facts

Active ingredient

Isopropyl alcohol (70% conc.)

Purpose

First aid antiseptic

Uses

- first aid to help prevent the risk of infection in minor cuts, scrapes and burns

Warnings

For external use only

- flammable, keep away from fire or flame
- if taken internally serious gastric disturbances will result

Ask a doctor before use if you have

- deep puncture wounds, animal bites or serious burns

When using this product

- do not get into eyes
- do not apply over large areas of the body
- do not use longer than one week unless directed by a doctor
- do not use otherwise than directed

Stop use and ask a doctor if

- condition persists or gets worse

Keep out of reach of children.

In case of ingestion, get medical help or contact a Poison Control Center (1-800-222-1222) immediately.

Directions

- clean affected area
- apply small amount of this product on the area 1-3 times daily
- if bandaged, let dry first
- may be covered with a sterile bandage

Other information

- store at room temperature
- does not contain, nor is intended as a substitute for grain or ethyl alcohol

Inactive ingredients

purified water

DISTRIBUTED BY:
Marlex Pharmaceuticals, Inc.
New Castle, DE 19720
Made in USA

Principal Display Panel

70% Isopropyl Alcohol
First Aid Antiseptic
Helps prevent the risk of infection in minor, cuts, scrapes and burns.
FL OZ (mL)
TAMPER EVIDENT: DO NOT USE IF PRINTED SAFETY FOIL UNDER THE CAP IS BROKEN OR MISSING.